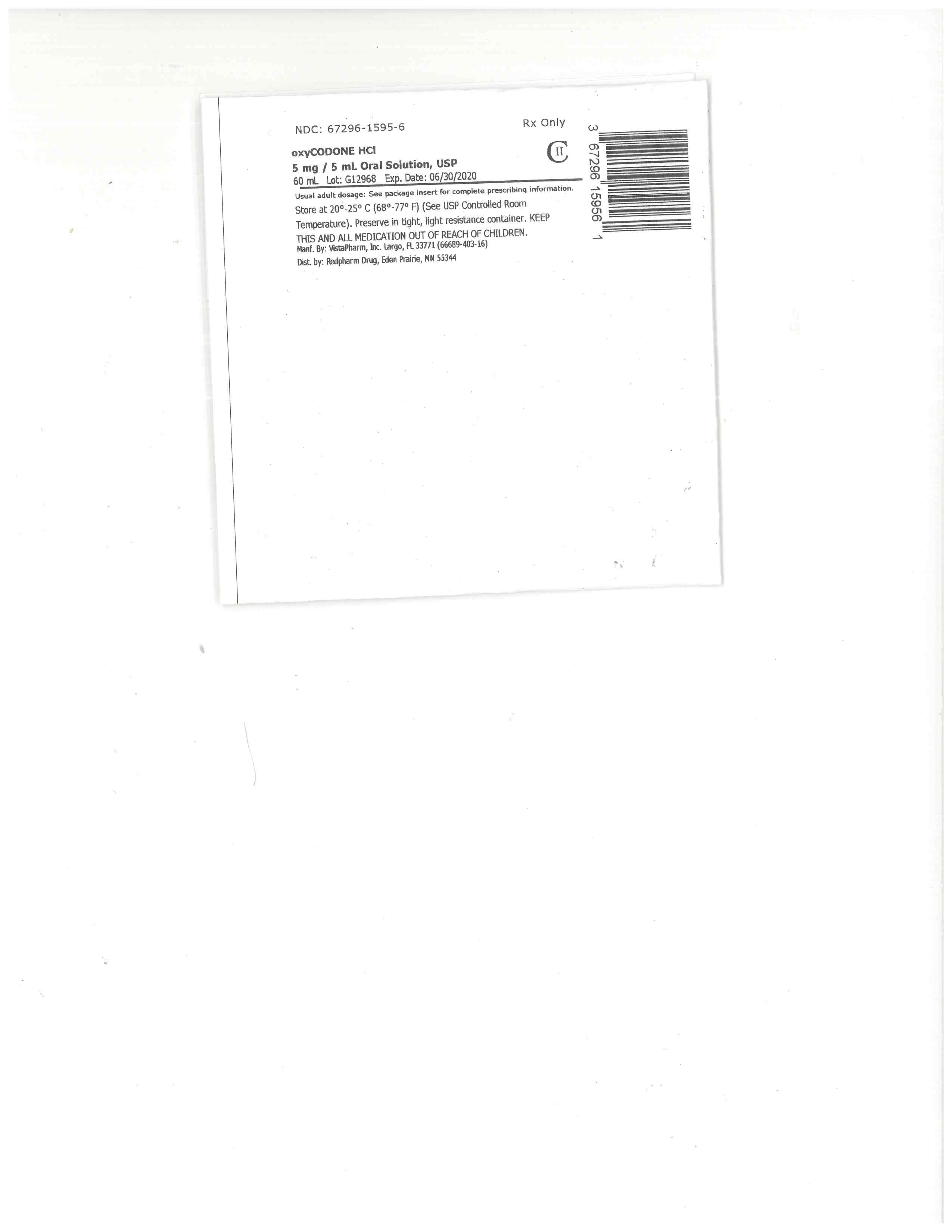 DRUG LABEL: Oxycodone Hydrochloride
NDC: 67296-1595 | Form: SOLUTION
Manufacturer: RedPharm Drug, Inc.
Category: prescription | Type: HUMAN PRESCRIPTION DRUG LABEL
Date: 20220121
DEA Schedule: CII

ACTIVE INGREDIENTS: OXYCODONE HYDROCHLORIDE 5 mg/5 mL
INACTIVE INGREDIENTS: SODIUM BENZOATE; POLOXAMER 188; GLYCERIN; WATER; FD&C RED NO. 40; RASPBERRY; ANHYDROUS CITRIC ACID; SORBITOL

oxy soln

BOXED WARNING

WARNING: RISK OF MEDICATION ERRORS; ADDICTION, ABUSE AND MISUSE; LIFE-THREATENING RESPIRATORY DEPRESSION; ACCIDENTAL INGESTION; NEONATAL OPIOID WITHDRAWAL SYNDROME; CYTOCHROME P450 3A4 INTERACTION; and RISKS FROM CONCOMITANT USE WITH BENZODIAZEPINES OR OTHER CNS DEPRESSANTS

Risk of Medication Errors

Ensure accuracy when prescribing, dispensing, and administering Oxycodone Hydrochloride Oral Solution. Dosing errors due to confusion between mg and mL, and other oxycodone hydrochloride oral solutions of different concentrations can result in accidental overdose and death [see Dosage and Administration (2.1), Warnings and Precautions (5.1) ].

Addiction, Abuse, and Misuse

Oxycodone Hydrochloride Oral Solution exposes patients and other users to the risks of opioid addiction, abuse, and misuse, which can lead to overdose and death. Assess each patient’s risk prior to prescribing Oxycodone Hydrochloride Oral Solution, and monitor all patients regularly for the development of these behaviors and conditions [see Warnings and Precautions (5.2) ] .

Life-Threatening Respiratory Depression

Serious, life-threatening, or fatal respiratory depression may occur with use of Oxycodone Hydrochloride Oral Solution. Monitor for respiratory depression, especially during initiation of Oxycodone Hydrochloride Oral Solution or following a dose increase [see Warnings and Precautions (5.3) ].

Accidental Ingestion

Accidental ingestion (or exposure) of even one dose of Oxycodone Hydrochloride Oral Solution, especially by children, can result in a fatal overdose of oxycodone [see Warnings and Precautions (5.3) ] .

Neonatal Opioid Withdrawal Syndrome

Prolonged use of Oxycodone Hydrochloride Oral Solution during pregnancy can result in neonatal opioid withdrawal syndrome, which may be life-threatening if not recognized and treated, and requires management according to protocols developed by neonatology experts. If opioid use is required for a prolonged period in a pregnant woman, advise the patient of the risk of neonatal opioid withdrawal syndrome and ensure that appropriate treatment will be available [see Warnings and Precautions (5.4) ].

Cytochrome P450 3A4 Interaction

The concomitant use of Oxycodone Hydrochloride Oral Solution with all cytochrome P450 3A4 inhibitors may result in an increase in oxycodone plasma concentrations, which could increase or prolong adverse reactions and may cause potentially fatal respiratory depression. In addition, discontinuation of a concomitantly used cytochrome P450 3A4 inducer may result in an increase in oxycodone plasma concentration. Monitor patients receiving Oxycodone Hydrochloride Oral Solution and any CYP3A4 inhibitor or inducer [see Warnings and Precautions (5.5), Drug Interactions (7), Clinical Pharmacology (12.3) ].

Risks From Concomitant Use With Benzodiazepines Or Other CNS Depressants Concomitant use of opioids with benzodiazepines or other central nervous system (CNS) depressants, including alcohol, may result in profound sedation, respiratory depression, coma, and death [see Warnings and Precautions (5.6), Drug Interactions (7) ] .

Reserve concomitant prescribing of Oxycodone Hydrochloride Oral Solution and benzodiazepines or other CNS depressants for use in patients for whom alternative treatment options are inadequate.
Limit dosages and durations to the minimum required.
Follow patients for signs and symptoms of respiratory depression and sedation.

HIGHLIGHTS OF PRESCRIBING INFORMATION

These highlights do not include all the information needed to use OXYCODONE HYDROCHLORIDE ORAL SOLUTION safely and effectively. See full prescribing information for OXYCODONE HYDROCHLORIDE ORAL SOLUTION.
Oxycodone Hydrochloride oral solution CII
Initial U.S. Approval: 1950

WARNING: RISK OF MEDICATION ERRORS; ADDICTION, ABUSE, AND MISUSE; LIFE-THREATENING RESPIRATORY DEPRESSION; ACCIDENTAL INGESTION; NEONATAL OPIOID WITHDRAWAL SYNDROME; CYTOCHROME P450 3A4 INTERACTION; AND RISKS FROM CONCOMITANT USE WITH BENZODIAZEPINES OR OTHER CNS DEPRESSANTS
SEE FULL PRESCRIBING INFORMATION FOR COMPLETE BOXED WARNING.

Ensure accuracy when prescribing, dispensing, and administering Oxycodone Hydrochloride Oral Solution. Dosing errors due to confusion between mg and mL, and other Oxycodone Hydrochloride Oral Solution of different concentrations can result in accidental overdose and death. (2.1, 5.1)
Oxycodone Hydrochloride Oral Solution exposes users to risks of addiction, abuse, and misuse, which can lead to overdose and death. Assess patient’s risk before prescribing and monitor regularly for these behaviors and conditions. (5.2)
Serious, life-threatening, or fatal respiratory depression may occur. Monitor closely, especially upon initiation or following a dose increase. (5.3)
Accidental ingestion of Oxycodone Hydrochloride Oral Solution, especially by children, can result in a fatal overdose of oxycodone. (5.3)
Prolonged use of Oxycodone Hydrochloride Oral Solution during pregnancy can result in neonatal opioid withdrawal syndrome, which may be life-threatening if not recognized and treated. If prolonged opioid use is required in a pregnant woman, advise the patient of the risk of neonatal opioid withdrawal syndrome and ensure that appropriate treatment will be available. (5.4)
Concomitant use with CYP3A4 inhibitors (or discontinuation of CYP3A4 inducers) can result in a fatal overdose of oxycodone. (5.5, 7, 12.3)
Concomitant use of opioids with benzodiazepines or other central nervous system (CNS) depressants, including alcohol, may result in profound sedation, respiratory depression, coma, and death. Reserve concomitant prescribing for use in patients for whom alternative treatment options are inadequate; limit dosages and durations to the minimum required; and follow patients for signs and symptoms of respiratory depression and sedation. (5.6, 7)

RECENT MAJOR CHANGES

BOXED WARNING

INDICATIONS AND USAGE 12/2016

DOSAGE AND ADMINISTRATION 12/2016

WARNINGS AND PRECAUTIONS 12/2016

INDICATIONS AND USAGE

Oxycodone Hydrochloride Oral Solution is an opioid agonist indicated for the management of pain severe enough to require an opioid-analgesic and for which alternative treatments are inadequate. (1)

Limitations of Use (1)

Because of the risks of addiction, abuse, and misuse with opioids, even at recommended doses, reserve Oxycodone Hydrochloride Oral Solution for use in patients for whom alternative treatment options [e.g., non-opioid analgesics or opioid combination products]:

Have not been tolerated, or are not expected to be tolerated,
Have not provided adequate analgesia, or are not expected to provide adequate analgesia

DOSAGE AND ADMINISTRATION

Use the lowest effective dosage for the shortest duration consistent with individual patient treatment goals. (2.1).
Individualize dosing based on the severity of pain, patient response, prior analgesic experience, and risk factors for addiction, abuse, and misuse. (2.1)
Initiate dosing with a range of 5 to 15 mg every 4 to 6 hours as needed for pain. (2.2).
For control of chronic pain, administer Oxycodone Hydrochloride Oral Solution on a regularly scheduled basis, at the lowest dosage level to achieve adequate analgesia. (2.2)
Individually titrate Oxycodone Hydrochloride Oral Solution to a dose that provides adequate analgesia and minimizes adverse reactions. (2.3)
Do not stop Oxycodone Hydrochloride Oral Solution abruptly in a physically-dependent patient. (2.4)

DOSAGE FORMS AND STRENGTHS

Oral solution 5 mg per 5 mL (1 mg/mL) (3)

CONTRAINDICATIONS

Significant respiratory depression. (4)
Acute or severe bronchial asthma in an unmonitored setting or in absence of resuscitative equipment. (4)
Known or suspected gastrointestinal obstruction, including paralytic ileus. (4)
Hypersensitivity to oxycodone. (4)

WARNINGS AND PRECAUTIONS

Life-Threatening Respiratory Depression in Patients with Chronic Pulmonary Disease or in Elderly, Cachectic, or Debilitated Patients: Monitor closely, particularly during initiation and titration. (5.7)
Adrenal Insufficiency: If diagnosed, treat with physiologic replacement of corticosteroids, and wean patient off of the opioid. (5.8)
Severe Hypotension: Monitor during dosage initiation and titration. Avoid use of Oxycodone Hydrochloride Oral Solution in patients with circulatory shock. (5.9)
Risks of Use in Patients with Increased Intracranial Pressure, Brain Tumors, Head Injury, or Impaired Consciousness: Monitor for sedation and respiratory depression. Avoid use of Oxycodone Hydrochloride Oral Solution in patients with impaired consciousness or coma. (5.10)

ADVERSE REACTIONS

Most common adverse reactions are nausea, constipation, vomiting, headache, pruritus, insomnia, dizziness, asthenia, and somnolence. (6)

To report SUSPECTED ADVERSE REACTIONS, contact VistaPharm Inc. at 1-727-530-1633, or FDA at 1-800-FDA-1088 or WWW.FDA.GOV/MEDWATCH.

DRUG INTERACTIONS

Serotonergic Drugs: Concomitant use may result in serotonin syndrome. Discontinue Oxycodone Hydrochloride Oral Solution if serotonin syndrome is suspected. (7)
Monoamine Oxidase Inhibitors (MAOIs): Can potentiate the effects of oxycodone. Avoid concomitant use in patients receiving MAOIs or within 14 days of stopping treatment with an MAOI. (7)
Mixed Agonist/Antagonist and Partial Agonist Opioid Analgesics: Avoid use with Oxycodone Hydrochloride Oral Solution because they may reduce analgesic effect of Oxycodone Hydrochloride Oral Solution or precipitate withdrawal symptoms. (7)

USE IN SPECIFIC POPULATIONS

Pregnancy: May cause fetal harm. (8.1)

See 17 for PATIENT COUNSELING INFORMATION and Medication Guide.

Revised: 12/2016

FULL PRESCRIBING INFORMATION: CONTENTS*

1 INDICATIONS AND USAGE
2 DOSAGE AND ADMINISTRATION
2.1 Important Dosage and Administration Instructions
2.2 Initial Dosage
2.3 Titration and Maintenance of Therapy
2.4 Discontinuation of Oxycodone Hydrochloride Oral Solution
3 DOSAGE FORMS AND STRENGTHS
4 CONTRAINDICATIONS
5 WARNINGS AND PRECAUTIONS
5.1 Risk of Accidental Overdose and Death Due to Medication Errors
5.2 Addiction, Abuse and Misuse
5.3 Life-Threatening Respiratory Depression
5.4 Neonatal Opioid Withdrawal Syndrome
5.5 Risks of Concomitant Use or Discontinuation of Cytochrome P450 3A4 Inhibitors and Inducers
5.6 Risks from Concomitant Use with Benzodiazepines or Other CNS Depressants
5.7 Life-Threatening Respiratory Depression in Patients with Chronic Pulmonary Disease
or in Elderly, Cachectic, or Debilitated Patients
5.8 Adrenal Insufficiency
5.9 Severe Hypotension
5.10 Risks of Use in Patients with Increased Intracranial Pressure, Brain Tumors, Head Injury, or Impaired Consciousness
5.11 Risks of Use in Patients with Gastrointestinal Conditions
5.12 Increased Risk of Seizures in Patients with Seizure Disorders
5.13 Withdrawal
5.14 Risks of Driving and Operating Machinery
6 ADVERSE REACTIONS
7 DRUG INTERACTIONS
8 USE IN SPECIFIC POPULATIONS
8.1 Pregnancy
8.2 Lactation
8.3 Females and Males of Reproductive Potential
8.4 Pediatric Use
8.5 Geriatric Use
8.6 Hepatic Impairment
8.7 Renal Impairment
9 DRUG ABUSE AND DEPENDENCE
9.1 Controlled Substance
9.2 Abuse
9.3 Dependence
10 OVERDOSAGE
11 DESCRIPTION
12 CLINICAL PHARMACOLOGY
12.1 Mechanism of Action
12.2 Pharmacodynamics
12.3 Pharmacokinetics
13 NONCLINICAL TOXICOLOGY
13.1 Carcinogenesis, Mutagenesis, Impairment of Fertility
16 HOW SUPPLIED/STORAGE AND HANDLING
17 PATIENT COUNSELING INFORMATION

*
Sections or subsections omitted from the full prescribing information are not listed.

1 INDICATIONS AND USAGE

Oxycodone Hydrochloride Oral Solution is indicated for the management of pain severe enough to require an opioid analgesic and for which alternative treatments are inadequate.

Limitations of Use

Because of the risks of addiction, abuse, and misuse with opioids, even at recommended doses [seeWarnings and Precautions (5.2) ], reserve Oxycodone Hydrochloride Oral Solution for use in patients for whom alternative treatment options [e.g., non-opioid analgesics or opioid combination products]:

Have not been tolerated, or are not expected to be tolerated,
Have not provided adequate analgesia, or are not expected to provide adequate analgesia

2 DOSAGE AND ADMINISTRATION

2.1 Important Dosage and Administration Instructions

Ensure accuracy when prescribing, dispensing, and administering Oxycodone Hydrochloride Oral Solution to avoid dosing errors due to confusion between mg and mL, and with other oxycodone hydrochloride solutions of different concentrations, which could result in accidental overdose and death. Ensure the proper dose is communicated and dispensed. When writing prescriptions, include both the total dose in mg and the total dose in volume.

Always use the enclosed calibrated measuring cup when administering Oxycodone Hydrochloride Oral Solution 5 mg/5 mL (1 mg/mL), to ensure that the dose is measured and administered accurately.

Do not use household teaspoons or tablespoons to measure Oxycodone Hydrochloride Oral Solution, as using a tablespoon instead of a teaspoon could lead to overdosage.

Use the lowest effective dosage for the shortest duration consistent with individual patient treatment goals [see Warnings and Precautions (5) ] .

Initiate the dosing regimen for each patient individually, taking into account the patient's severity of pain, patient response, prior analgesic treatment experience, and risk factors for addiction, abuse, and misuse [see Warnings and Precautions (5.2) ].

Monitor patients closely for respiratory depression, especially within the first 24-72 hours of initiating therapy and following dosage increases with oxycodone hydrochloride solution and adjust the dosage accordingly [see Warnings and Precautions (5.3) ].

2.2 Initial Dosage

Use of Oxycodone Hydrochloride Oral Solution as the First Opioid Analgesic

Initiate treatment with Oxycodone Hydrochloride Oral Solution: 5 to 15 mg every 4 to 6 hours as needed for pain.

For control of severe chronic pain, Oxycodone Hydrochloride Oral Solution should be administered on a regularly scheduled basis, every 4 to 6 hours, at the lowest dosage level that will achieve adequate analgesia.

As with any opioid drug product, adjust the dosing regimen for each patient individually, taking into account the patient's prior analgesic treatment experience. In the selection of the initial dose of oxycodone hydrochloride, give attention to the following:

the total daily dose, potency and specific characteristics of the opioid the patient has been taking previously;
the reliability of the relative potency estimate used to calculate the equivalent oxycodone hydrochloride dose needed; the patient's degree of opioid tolerance;
the general condition and medical status of the patient;
concurrent medications;
the type and severity of the patient's pain;
risk factors for abuse, addiction or diversion, including a prior history of abuse, addiction or diversion.

The following dosing recommendations, therefore, can only be considered as suggested approaches to what is actually a series of clinical decisions over time in the management of the pain of each individual patient.

Continual re-evaluation of the patient receiving oxycodone hydrochloride is important, with special attention to the maintenance of pain management and the relative incidence of side effects associated with therapy. During chronic therapy, especially for non-cancer-related pain, periodically re-assess the continued need for the use of opioid analgesics.

During periods of changing analgesic requirements, including initial titration, frequent contact is recommended between physician, other members of the healthcare team, the patient, and the caregiver/family.

Conversion from Other Opioids to Oxycodone Hydrochloride Oral Solution

There is inter-patient variability in the potency of opioid drugs and opioid formulations. Therefore, a conservative approach is advised when determining the total daily dosage of Oxycodone Hydrochloride Oral Solution. It is safer to underestimate a patient’s 24-hour Oxycodone Hydrochloride Oral Solution than to overestimate the 24-hour Oxycodone Hydrochloride Oral Solution dosage and manage an adverse reaction due to overdose.

Consider the following general points regarding opioid conversions.

In converting patients from other opioids to Oxycodone Hydrochloride Oral Solution, close observation and adjustment of dosage based upon the patient’s response to Oxycodone Hydrochloride Oral Solution is imperative. Physicians and other healthcare professionals are advised to refer to published relative potency information, keeping in mind that conversion ratios are only approximate.

Conversion from Oxycodone Hydrochloride Oral Solution to Extended-Release oxycodone

The relative bioavailability of Oxycodone Hydrochloride Oral Solution compounds to extended -release oxycodone is unknown, so conversion to extended-release tablets/capsules must be accompanied by close observation for signs of excessive sedation and respiratory depression.

2.3 Titration and Maintenance of Therapy

Individually titrate Oxycodone Hydrochloride Oral Solution to a dose that provides adequate analgesia and minimizes adverse reactions. Continually reevaluate patients receiving Oxycodone Hydrochloride Oral Solution to assess the maintenance of pain control and the relative incidence of adverse reactions, as well as monitoring for the development of addiction, abuse, or misuse [see Warnings and Precautions (5.2) ]. Frequent communication is important among the prescriber, other members of the healthcare team, the patient, and the caregiver/family during periods of changing analgesic requirements, including initial titration.

If the level of pain increases after dosage stabilization, attempt to identify the source of increased pain before increasing the Oxycodone Hydrochloride Oral Solution dosage. If unacceptable opioid-related adverse reactions are observed, consider reducing the dosage. Adjust the dosage to obtain an appropriate balance between management of pain and opioid-related adverse reactions.

2.4 Discontinuation of Oxycodone Hydrochloride Oral Solution

When a patient who has been taking Oxycodone Hydrochloride Oral Solution regularly and may be physically dependent no longer requires therapy with cocaine hydrochloride oral solution, taper the dose gradually, by 25% to 50% every 2 to 4 days, while monitoring carefully for signs and symptoms of withdrawal. If the patient develops these signs or symptoms, raise the dose to the previous level and taper more slowly, either by increasing the interval between decreases, decreasing the amount of change in dose, or both. Do not abruptly discontinue Oxycodone Hydrochloride Oral Solution in a physically-dependent patient [see Warnings and Precautions (5.13), Drug Abuse and Dependence (9.3) ] .

3 DOSAGE FORMS AND STRENGTHS

Oxycodone Hydrochloride Oral Solution, USP

5 mg per 5 mL (1 mg /mL)

4 CONTRAINDICATIONS

Oxycodone Hydrochloride Oral Solution is contraindicated in patients with:

Significant respiratory depression [ see Warnings and Precautions (5.3) ]
Acute or severe bronchial asthma in an unmonitored setting or in the absence of resuscitative equipment [see Warnings and Precautions (5.3)]
Known or suspected gastrointestinal obstruction, including paralytic ileus [see Warnings and Precautions (5.11) ]
Hypersensitivity to oxycodone [see Warnings and Precautions (5.1) , Adverse Reactions (6) ]

5 WARNINGS AND PRECAUTIONS

5.1 Risk of Accidental Overdose and Death Due to Medication Errors

Dosing errors can result in accidental overdose and death. Avoid dosing errors that may result from confusion between mg and mL and confusion with oxycodone solutions of different concentrations, when prescribing, dispensing, and administering Oxycodone Hydrochloride Oral Solution. Ensure that the dose is communicated clearly and dispensed accurately. Always use the enclosed calibrated measuring cup when administering Oxycodone Hydrochloride Oral Solution to ensure the dose is measured and administered accurately. Do not use a teaspoon or a tablespoon to measure a dose. A household teaspoon or tablespoon is not an adequate measuring device. Given the inexactitude of the household spoon measure and the possibility of using a tablespoon instead of a teaspoon, which could lead to overdosage, it is strongly recommended that, if the enclosed calibrated measuring cup becomes lost, caregivers obtain and use a calibrated measuring device. Health care providers should recommend a calibrated device that can measure and deliver the prescribed dose accurately, and instruct caregivers to use extreme caution in measuring the dosage.

5.2 Addiction, Abuse and Misuse

Oxycodone Hydrochloride Oral Solution contains oxycodone, a Schedule II controlled substance. As an opioid, Oxycodone Hydrochloride Oral Solution exposes users to the risks of addiction, abuse, and misuse [see Drug Abuse and Dependence (9) ].

Although the risk of addiction in any individual is unknown, it can occur in patients appropriately prescribed Oxycodone Hydrochloride Oral Solution. Addiction can occur at recommended dosages and if the drug is misused or abused.

Assess each patient’s risk for opioid addiction, abuse, or misuse prior to prescribing Oxycodone Hydrochloride Oral Solution, and monitor all patients receiving Oxycodone Hydrochloride Oral Solution for the development of these behaviors and conditions. Risks are increased in patients with a personal or family history of substance abuse (including drug or alcohol abuse or addiction) or mental illness (e.g., major depression). The potential for these risks should not, however, prevent the proper management of pain in any given patient. Patients at increased risk may be prescribed opioids such as Oxycodone Hydrochloride Oral Solution, but use in such patients necessitates intensive counseling about the risks and proper use of Oxycodone Hydrochloride Oral Solution along with intensive monitoring for signs of addiction, abuse, and misuse.

Opioids are sought by drug abusers and people with addiction disorders and are subject to criminal diversion. Consider these risks when prescribing or dispensing Oxycodone Hydrochloride Oral Solution. Strategies to reduce these risks include prescribing the drug in the smallest appropriate quantity and advising the patient on the proper disposal of unused drug [see Patient Counseling Information (17) ]. Contact local state professional licensing board or state controlled substances authority for information on how to prevent and detect abuse or diversion of this product.

5.3 Life-Threatening Respiratory Depression

Serious, life-threatening, or fatal respiratory depression has been reported with the use of opioids, even when used as recommended. Respiratory depression, if not immediately recognized and treated, may lead to respiratory arrest and death. Management of respiratory depression may include close observation, supportive measures, and use of opioid antagonists, depending on the patient’s clinical status [see Overdosage (10)]. Carbon dioxide (CO 2) retention from opioid-induced respiratory depression can exacerbate the sedating effects of opioids.

While serious, life-threatening, or fatal respiratory depression can occur at any time during the use of Oxycodone Hydrochloride Oral Solution, the risk is greatest during the initiation of therapy or following a dosage increase. Monitor patients closely for respiratory depression, especially within the first 24-72 hours of initiating therapy with and following dosage increases of Oxycodone Hydrochloride Oral Solution.

To reduce the risk of respiratory depression, proper dosing and titration of Oxycodone Hydrochloride Oral Solution are essential [see Dosage and Administration (2) ]. Overestimating the Oxycodone Hydrochloride Oral Solution dosage when converting patients from another opioid product can result in a fatal overdose with the first dose.

Accidental ingestion of even one dose of Oxycodone Hydrochloride Oral Solution, especially by (in) children, can result in respiratory depression and death due to an overdose of oxycodone.

5.4 Neonatal Opioid Withdrawal Syndrome

Prolonged use of Oxycodone Hydrochloride Oral Solution during pregnancy can result in withdrawal in the neonate. Neonatal opioid withdrawal syndrome, unlike opioid withdrawal syndrome in adults, may be life-threatening if not recognized and treated, and requires management according to protocols developed by neonatology experts. Observe newborns for signs of neonatal opioid withdrawal syndrome and manage accordingly. Advise pregnant women using opioids for a prolonged period of the risk of neonatal opioid withdrawal syndrome and ensure that appropriate treatment will be available [see Use in Specific Populations (8.1), Patient Counseling Information ] .

5.5 Risks of Concomitant Use or Discontinuation of Cytochrome P450 3A4 Inhibitors and Inducers

Concomitant use of Oxycodone Hydrochloride Oral Solution with a CYP3A4 inhibitor, such as macrolide antibiotics (e.g., erythromycin), azole-antifungal agents (e.g., ketoconazole), and protease inhibitors (e.g., ritonavir), may increase plasma concentrations of oxycodone and prolong opioid adverse reactions, which may cause potentially fatal respiratory depression [see Warnings and Precautions (5.3) ], particularly when an inhibitor is added after a stable dose of Oxycodone Hydrochloride Oral Solution is achieved. Similarly, discontinuation of a CYP3A4 inducer, such as rifampin, carbamazepine, and phenytoin, in Oxycodone Hydrochloride Oral Solution-treated patients may increase oxycodone plasma concentrations and prolong opioid adverse reactions. When using Oxycodone Hydrochloride Oral Solution with CYP3A4 inhibitors or discontinuing CYP3A4 inducers in Oxycodone Hydrochloride Oral Solution-treated patients, monitor patients closely at frequent intervals and consider dosage reduction of Oxycodone Hydrochloride Oral Solution until stable drug effects are achieved [see Dosage and Administration (2.1), Drug Interactions (7) ].

Concomitant use of Oxycodone Hydrochloride Oral Solution with CYP3A4 inducers or discontinuation of an CYP3A4 inhibitor could decrease oxycodone plasma concentrations, decrease opioid efficacy or, possibly, lead to a withdrawal syndrome in a patient who had developed physical dependence to oxycodone. When using Oxycodone Hydrochloride Oral Solution with CYP3A4 inducers or discontinuing CYP3A4 inhibitors, monitor patients closely at frequent intervals and consider increasing the opioid dosage if needed to maintain adequate analgesia or if symptoms of opioid withdrawal occur [see Dosage and Administration (2.1), Drug Interactions (7) ].

5.6 Risks from Concomitant Use with Benzodiazepines or Other CNS Depressants

Profound sedation, respiratory depression, coma, and death may result from the concomitant use of Oxycodone Hydrochloride Oral Solution with benzodiazepines or other CNS depressants (e.g., non-benzodiazepine sedatives/hypnotics, anxiolytics, tranquilizers, muscle relaxants, general anesthetics, antipsychotics, other opioids, alcohol). Because of these risks, reserve concomitant prescribing of these drugs for use in patients for whom alternative treatment options are inadequate.

Observational studies have demonstrated that concomitant use of opioid analgesics and benzodiazepines increases the risk of drug-related mortality compared to use of opioid analgesics alone. Because of similar pharmacological properties, it is reasonable to expect similar risk with the concomitant use of other CNS depressant drugs with opioid analgesics [see Drug Interactions (7) ] .

If the decision is made to prescribe a benzodiazepine or other CNS depressant concomitantly with an opioid analgesic, prescribe the lowest effective dosages and minimum durations of concomitant use. In patients already receiving an opioid analgesic, prescribe a lower initial dose of the benzodiazepine or other CNS depressant than indicated in the absence of an opioid, and titrate based on clinical response. If an opioid analgesic is initiated in a patient already taking a benzodiazepine or other CNS depressant, prescribe a lower initial dose of the opioid analgesic, and titrate based on clinical response. Follow patients closely for signs and symptoms of respiratory depression and sedation.

Advise both patients and caregivers about the risks of respiratory depression and sedation when Oxycodone Hydrochloride Oral Solution is used with benzodiazepines or other CNS depressants (including alcohol and illicit drugs). Advise patients not to drive or operate heavy machinery until the effects of concomitant use of the benzodiazepine or other CNS depressant have been determined. Screen patients for risk of substance use disorders, including opioid abuse and misuse, and warn them of the risk for overdose and death associated with the use of additional CNS depressants including alcohol and illicit drugs [see Drug Interactions (7) and Patient Counseling Information (17) ] .

5.7 Life-Threatening Respiratory Depression in Patients with Chronic Pulmonary Disease
or in Elderly, Cachectic, or Debilitated Patients

The use of Oxycodone Hydrochloride Oral Solution in patients with acute or severe bronchial asthma in an unmonitored setting or in the absence of resuscitative equipment is contraindicated.

Patients with Chronic Pulmonary Disease: Oxycodone Hydrochloride Oral Solution-treated patients with significant chronic obstructive pulmonary disease or cor pulmonale, and those with a substantially decreased respiratory reserve, hypoxia, hypercapnia, or pre-existing respiratory depression are at increased risk of decreased respiratory drive including apnea, even at recommended dosages of Oxycodone Hydrochloride Oral Solution [see Warnings and Precautions (5.3) ].

Elderly, Cachetic, or Debilitated Patients: Life-threatening respiratory depression is more likely to occur in elderly, cachectic, or debilitated patients because they may have altered pharmacokinetics or altered clearance compared to younger, healthier patients [see Warnings and Precautions (5.3) ].

Monitor such patients closely, particularly when initiating and titrating Oxycodone Hydrochloride Oral Solution and when Oxycodone Hydrochloride Oral Solution is given concomitantly with other drugs that depress respiration [see Warnings and Precautions (5.3) ]. Alternatively, consider the use of non-opioid analgesics in these patients.

5.8 Adrenal Insufficiency

Cases of adrenal insufficiency have been reported with opioid use, more often following greater than one month of use. Presentation of adrenal insufficiency may include non-specific symptoms and signs including nausea, vomiting, anorexia, fatigue, weakness, dizziness, and low blood pressure. If adrenal insufficiency is suspected, confirm the diagnosis with diagnostic testing as soon as possible. If adrenal insufficiency is diagnosed, treat with physiologic replacement doses of corticosteroids. Wean the patient off of the opioid to allow adrenal function to recover and continue corticosteroid treatment until adrenal function recovers. Other opioids may be tried as some cases reported use of a different opioid without recurrence of adrenal insufficiency. The information available does not identify any particular opioids as being more likely to be associated with adrenal insufficiency.

5.9 Severe Hypotension

Oxycodone Hydrochloride Oral Solution may cause severe hypotension including orthostatic hypotension and syncope in ambulatory patients. There is increased risk in patients whose ability to maintain blood pressure has already been compromised by a reduced blood volume or concurrent administration of certain CNS depressant drugs (e.g. phenothiazines or general anesthetics) [see Drug Interactions (7) ]. Monitor these patients for signs of hypotension after initiating or titrating the dosage of Oxycodone Hydrochloride Oral Solution. In patients with circulatory shock, Oxycodone Hydrochloride Oral Solution may cause vasodilation that can further reduce cardiac output and blood pressure. Avoid the use of Oxycodone Hydrochloride Oral Solution in patients with circulatory shock.

5.10 Risks of Use in Patients with Increased Intracranial Pressure, Brain Tumors, Head Injury, or Impaired Consciousness

In patients who may be susceptible to the intracranial effects of CO 2 retention (e.g., those with evidence of increased intracranial pressure or brain tumors), Oxycodone Hydrochloride Oral Solution may reduce respiratory drive, and the resultant CO 2 retention can further increase intracranial pressure. Monitor such patients for signs of sedation and respiratory depression, particularly when initiating therapy with Oxycodone Hydrochloride Oral Solution.

Opioids may also obscure the clinical course in a patient with a head injury. Avoid the use of Oxycodone Hydrochloride Oral Solution in patients with impaired consciousness or coma.

5.11 Risks of Use in Patients with Gastrointestinal Conditions

Oxycodone Hydrochloride Oral Solution is contraindicated in patients with known or suspected gastrointestinal obstruction, including paralytic ileus.

The oxycodone in Oxycodone Hydrochloride Oral Solution may cause spasm of the sphincter of Oddi. Opioids may cause increases in serum amylase. Monitor patients with biliary tract disease, including acute pancreatitis for worsening symptoms.

5.12 Increased Risk of Seizures in Patients with Seizure Disorders

The oxycodone in Oxycodone Hydrochloride Oral Solution may increase the frequency of seizures in patients with seizure disorders, and may increase the risk of seizures occurring in other clinical settings associated with seizures. Monitor patients with a history of seizure disorders for worsened seizure control during Oxycodone Hydrochloride Oral Solution therapy.

5.13 Withdrawal

Avoid the use of mixed agonist/antagonist (e.g., pentazocine, nalbuphine, and butorphanol) or partial agonist (e.g., buprenorphine) analgesics in patients who are receiving a full opioid agonist analgesic, including Oxycodone Hydrochloride Oral Solution. In these patients, mixed agonist/antagonist and partial agonist analgesics may reduce the analgesic effect and/or precipitate withdrawal symptoms [see Drug Interactions (7) ].

When discontinuing Oxycodone Hydrochloride Oral Solution in a physically-dependent patient, gradually taper the dosage [see Dosage and Administration (2.1) ]. Do not abruptly discontinue Oxycodone Hydrochloride Oral Solution in these patients [see Drug Abuse and Dependence (9.3) ].

5.14 Risks of Driving and Operating Machinery

Oxycodone Hydrochloride Oral Solution may impair the mental or physical abilities needed to perform potentially hazardous activities such as driving a car or operating machinery. Warn patients not to drive or operate dangerous machinery unless they are tolerant to the effects of Oxycodone Hydrochloride Oral Solution and know how they will react to the medication [see Patient Counseling Information (17) ].

6 ADVERSE REACTIONS

The following serious adverse reactions are described, or described in greater detail, in other sections:

Addiction, Abuse, and Misuse [see Warnings and Precautions (5.2) ]
Life-Threatening Respiratory Depression [see Warnings and Precautions (5.3) ]
Neonatal Opioid Withdrawal Syndrome [see Warnings and Precautions (5.4) ]
Interactions with Benzodiazepines or Other CNS Depressants [see Warnings and Precautions (5.6) ]
Adrenal Insufficiency [see Warnings and Precautions (5.8) ]
Severe Hypotension [see Warnings and Precautions (5.9) ]
Gastrointestinal Adverse Reactions [see Warnings and Precautions (5.11)]
Seizures [see Warnings and Precautions (5.12) ]
Withdrawal [see Warnings and Precautions (5.13) ]

The following adverse reactions associated with the use of oxycodone were identified in clinical studies or postmarketing reports. Because some of these reactions were reported voluntarily from a population of uncertain size, it is not always possible to reliably estimate their frequency or establish a causal relationship to drug exposure.

Serious adverse reactions associated with oxycodone use included: respiratory depression, respiratory arrest, circulatory depression, cardiac arrest, hypotension, and/or shock.

The common adverse reactions seen on initiation of therapy with oxycodone are dose-related and are typical opioid-related adverse reactions. The most frequent adverse events include nausea, constipation, vomiting, headache, and pruritus. The frequency of these reactions depended on several factors, including clinical setting, the patient’s level of opioid tolerance, and host factors specific to the individual.

In all patients for whom dosing information was available (n = 191) from the open-label and double-blind studies involving another formulation of immediate-release oxycodone, the following adverse events were recorded in oxycodone treated patients with an incidence ≥ 3%. In descending order of frequency they were: nausea, constipation, vomiting, headache, pruritus, insomnia, dizziness, asthenia, and somnolence.

The other less frequently observed adverse reactions from opioid analgesics, including Oxycodone Hydrochloride Oral Solution included:

Body as a Whole: abdominal pain, accidental injury, allergic reaction, back pain, chills and fever, fever, flu syndrome, infection, neck pain, pain, photosensitivity reaction, and sepsis.

Cardiovascular: deep thrombophlebitis, heart failure, hemorrhage, hypotension, migraine, palpitation, and tachycardia.

Digestive: anorexia, diarrhea, dyspepsia, dysphagia, gingivitis, glossitis, and nausea and vomiting.

Hemic and Lymphatic: anemia and leukopenia.

Metabolic and Nutritional: edema, gout, hyperglycemia, iron deficiency anemia and peripheral edema.

Musculoskeletal: arthralgia, arthritis, bone pain, myalgia and pathological fracture.

Nervous: agitation, anxiety, confusion, dry mouth, hypertonia, hypesthesia, nervousness, neuralgia, personality disorder, tremor, and vasodilation.

Respiratory: bronchitis, cough increased, dyspnea, epistaxis, laryngismus, lung disorder, pharyngitis, rhinitis, and sinusitis.

Skin and Appendages: herpes simplex, rash, sweating, and urticaria.

Special Senses: amblyopia.

Urogenital: urinary tract infection

Serotonin syndrome: Cases of serotonin syndrome, a potentially life-threatening condition, have been reported during concomitant use of opioids with serotonergic drugs.

Adrenal insufficiency: Cases of adrenal insufficiency have been reported with opioid use, more often following greater than one month of use.

Anaphylaxis: Anaphylaxis has been reported with ingredients contained in Oxycodone Hydrochloride Oral Solution.

Androgen deficiency: Cases of androgen deficiency have occurred with chronic use of opioids [see Clinical Pharmacology (12.2)] .

7 DRUG INTERACTIONS

Table 1 includes clinically significant drug interactions with Oxycodone Hydrochloride Oral Solution.

Inhibitors of CYP3A4 and CYP2D6

Clinical Impact:

The concomitant use of Oxycodone Hydrochloride Oral Solution and CYP3A4 inhibitors can increase the plasma concentration of oxycodone, resulting in increased or prolonged opioid effects. These effects could be more pronounced with concomitant use of Oxycodone Hydrochloride Oral Solution and CYP2D6 and CYP3A4 inhibitors, particularly when an inhibitor is added after a stable dose of Oxycodone Hydrochloride Oral Solution is achieved [see Warnings and Precautions (5.5) ].

After stopping a CYP3A4 inhibitor, as the effects of the inhibitor decline, the oxycodone plasma concentration will decrease [see Clinical Pharmacology (12.3) ], resulting in decreased opioid efficacy or a withdrawal syndrome in patients who had developed physical dependence to oxycodone.

Intervention:

If concomitant use is necessary, consider dosage reduction of Oxycodone Hydrochloride Oral Solution until stable drug effects are achieved

Monitor patients for respiratory depression and sedation at frequent intervals.

If a CYP3A4 inhibitor is discontinued, consider increasing the Oxycodone Hydrochloride Oral Solution dosage until stable drug effects are achieved [seeDosage and Administration (2.2) ]. Monitor for signs of opioid withdrawal.

Examples

Macrolide antibiotics (e.g., erythromycin), azole-antifungal agents (e.g. ketoconazole), protease inhibitors (e.g., ritonavir)

CYP3A4 Inducers

Clinical Impact:

The concomitant use of Oxycodone Hydrochloride Oral Solution and CYP3A4 inducers can decrease the plasma concentration of oxycodone [see Clinical Pharmacology (12.3) ], resulting in decreased efficacy or onset of a withdrawal syndrome in patients who have developed physical dependence to oxycodone [seeWarnings and Precautions (5.5) ].

After stopping a CYP3A4 inducer, as the effects of the inducer decline, the oxycodone plasma concentration will increase [see Clinical Pharmacology (12.3) ], which could increase or prolong both the therapeutic effects and adverse reactions, and may cause serious respiratory depression.

Intervention:

If concomitant use is necessary, consider increasing the Oxycodone Hydrochloride Oral Solution dosage until stable drug effects are achieved. Monitor for signs of opioid withdrawal. If a CYP3A4 inducer is discontinued, consider Oxycodone Hydrochloride Oral Solution dosage reduction and monitor for signs of respiratory depression.

Examples

Rifampin, carbamazepine, phenytoin

Benzodiazepines and other Central Nervous System (CNS) Depressants

Clinical Impact:

Due to additive pharmacologic effect, the concomitant use of benzodiazepines or other CNS depressants including alcohol, increases the risk of respiratory depression, profound sedation, coma, and death.

Intervention:

Reserve concomitant prescribing of these drugs for use in patients for whom alternative treatment options are inadequate. Limit dosages and durations to the minimum required. Follow patients closely for signs of respiratory depression and sedation [see Warnings and Precautions (5.6) ] .

Examples:

Benzodiazepines and other sedatives/hypnotics, anxiolytics, tranquilizers, muscle relaxants, general anesthetics, antipsychotics, other opioids, alcohol.

Serotonergic Drugs

Clinical Impact:

The concomitant use of opioids with other drugs that affect the serotonergic neurotransmitter system has resulted in serotonin syndrome [see Warnings and Precautions (5.8) ] .

Intervention:

If concomitant use is warranted, carefully observe the patient, particularly during treatment initiation and dose adjustment. Discontinue Oxycodone Hydrochloride Oral Solution if serotonin syndrome is suspected.

Examples:

Selective serotonin reuptake inhibitors (SSRIs), serotonin and norepinephrine reuptake inhibitors (SNRIs), tricyclic antidepressants (TCAs), triptans, 5-HT3 receptor antagonists, drugs that affect the serotonin neurotransmitter system (e.g., mirtazapine, trazodone, tramadol), monoamine oxidase (MAO) inhibitors (those intended to treat psychiatric disorders and also others, such as linezolid and intravenous methylene blue).

Monoamine Oxidase Inhibitors (MAOIs)

Clinical Impact:

MAOI interactions with opioids may manifest as serotonin syndrome or opioid toxicity (e.g., respiratory depression, coma) [see Warnings and Precautions (5.3) ] .

Intervention:

The use of Oxycodone Hydrochloride Oral Solution is not recommended for patients taking MAOIs or within 14 days of stopping such treatment.

If urgent use of an opioid is necessary, use test doses and frequent titration of small doses to treat pain while closely monitoring blood pressure and signs and symptoms of CNS and respiratory depression.

Examples

phenelzine, tranylcypromine, linezolid

Mixed Agonist/Antagonist and Partial Agonist Opioid Analgesics

Clinical Impact:

May reduce the analgesic effect of Oxycodone Hydrochloride Oral Solution and/or precipitate withdrawal symptoms.

Intervention:

Avoid concomitant use.

Examples:

butorphanol, nalbuphine, pentazocine, buprenorphine

Muscle Relaxants

Clinical Impact:

Oxycodone may enhance the neuromuscular blocking action of skeletal muscle relaxants and produce an increased degree of respiratory depression.

Intervention:

Monitor patients for signs of respiratory depression that may be greater than otherwise expected and decrease the dosage of Oxycodone Hydrochloride Oral Solution and/or the muscle relaxant as necessary.

Diuretics

Clinical Impact:

Opioids can reduce the efficacy of diuretics by inducing the release of antidiuretic hormone.

Intervention:

Monitor patients for signs of diminished diuresis and/or effects on blood pressure and increase the dosage of the diuretic as needed.

Anticholinergic Drugs

Clinical Impact:

The concomitant use of anticholinergic drugs may increase risk of urinary retention and/or severe constipation, which may lead to paralytic ileus.

Intervention:

Monitor patients for signs of urinary retention or reduced gastric motility when Oxycodone Hydrochloride Oral Solution is used concomitantly with anticholinergic drugs.

8 USE IN SPECIFIC POPULATIONS

8.1 Pregnancy

Risk Summary

Prolonged use of opioid analgesics during pregnancy may cause neonatal opioid withdrawal syndrome [see Warnings and Precautions (5.3) ]. Available data with Oxycodone Hydrochloride Oral Solution are insufficient to inform a drug-associated risk for major birth defects and miscarriage.

Animal reproduction studies with oral administrations of oxycodone hydrochloride in rats and rabbits during the period of organogenesis at doses 2.6 and 8.1 times, respectively, the human dose of 60 mg/day did not reveal evidence of teratogenicity or embryo-fetal toxicity. In several published studies, treatment of pregnant rats with oxycodone at clinically relevant doses and below, resulted in neurobehavioral effects in offspring [see Data]. Based on animal data, advise pregnant women of the potential risk to a fetus.

The background risk of major birth defects and miscarriage for the indicated population is unknown. All pregnancies have a background risk of birth defect, loss, or other adverse outcomes. In the U.S. general population, the estimated background risk of major birth defects and miscarriage in clinically recognized pregnancies is 2-4% and 15-20%, respectively.

Clinical Considerations

Fetal/Neonatal Adverse Reactions

Prolonged use of opioid analgesics during pregnancy for medical or nonmedical purposes can result in physical dependence in the neonate and neonatal opioid withdrawal syndrome shortly after birth.

Neonatal opioid withdrawal syndrome presents as irritability, hyperactivity and abnormal sleep pattern, high pitched cry, tremor, vomiting, diarrhea, and failure to gain weight. The onset, duration, and severity of neonatal opioid withdrawal syndrome vary based on the specific opioid used, duration of use, timing and amount of last maternal use, and rate of elimination of the drug by the newborn. Observe newborns for symptoms of neonatal opioid withdrawal syndrome and manage accordingly [seeWarnings and Precautions (5.4) ].

Labor or Delivery

Opioids cross the placenta and may produce respiratory depression and psycho-physiologic effects in neonates. An opioid antagonist, such as naloxone, must be available for reversal of opioid-induced respiratory depression in the neonate. Oxycodone Hydrochloride Oral Solution is not recommended for use in pregnant women during or immediately prior to labor, when other analgesic techniques are more appropriate. Opioid analgesics, including Oxycodone Hydrochloride Oral Solution, can prolong labor through actions which temporarily reduce the strength, duration, and frequency of uterine contractions. However, this effect is not consistent and may be offset by an increased rate of cervical dilation, which tends to shorten labor. Monitor neonates exposed to opioid analgesics during labor for signs of excess sedation and respiratory depression.

Data

Animal Data

In embryo-fetal development studies in rats and rabbits, pregnant animals received oral doses of oxycodone hydrochloride administered during the period of organogenesis up to 16 mg/kg/day and up 25 mg/kg/day, respectively. These studies revealed no evidence of teratogenicity or embryo-fetal toxicity due to oxycodone. The highest doses tested in rats and rabbits were equivalent to approximately 2.6 and 8.1 times an adult human dose of 60 mg/day, respectively, on a mg/m 2 basis. In published studies, offspring of pregnant rats administered oxycodone during gestation have been reported to exhibit neurobehavioral effects including altered stress responses, increased anxiety-like behavior (2 mg/kg/day IV from Gestation Day 8 to 21 and Postnatal Day 1, 3, and 5; 0.3-times an adult human dose of 60 mg/day, on a mg/m 2 basis) and altered learning and memory (15 mg/kg/day orally from breeding through parturition; 2.4 times an adult human dose of 60 mg/day, on a mg/m 2 basis).

8.2 Lactation

Risk Summary

Oxycodone is present in breast milk. Published lactation studies report variable concentrations of oxycodone in breast milk with administration of immediate-release oxycodone to nursing mothers in the early postpartum period. The lactation studies did not assess breastfed infants for potential adverse reactions. Lactation studies have not been conducted with Oxycodone Hydrochloride Oral Solution, and no information is available on the effects of the drug on the breastfed infant or the effects of the drug on milk production.

The developmental and health benefits of breastfeeding should be considered along with the mother’s clinical need for Oxycodone Hydrochloride Oral Solution and any potential adverse effects on the breastfed infant from Oxycodone Hydrochloride Oral Solution or from the underlying maternal condition.

Clinical Considerations

Monitor infants exposed to Oxycodone Hydrochloride Oral Solution through breast milk for excess sedation and respiratory depression. Withdrawal symptoms can occur in breastfed infants when maternal administration of an opioid analgesic is stopped, or when breast-feeding is stopped.

8.3 Females and Males of Reproductive Potential

Infertility

Chronic use of opioids may cause reduced fertility in females and males of reproductive potential. It is not known whether these effects on fertility are reversible [see Adverse Reactions (6) , Clinical Pharmacology (12.2) ] .

8.4 Pediatric Use

The safety and efficacy of Oxycodone Hydrochloride Oral Solution in pediatric patients below the age of 18 have not been established.

8.5 Geriatric Use

Elderly patients (aged 65 years or older) may have increased sensitivity to oxycodone. In general, use caution when selecting a dose for an elderly patient, usually starting at the low end of the dosing range, reflecting the greater frequency of decreased hepatic, renal, or cardiac function and of concomitant disease or other drug therapy.

Respiratory depression is the chief risk for elderly patients treated with opioids, and has occurred after large initial doses were administered to patients who were not opioid-tolerant or when opioids were co-administered with other agents that depress respiration. Titrate the dosage of Oxycodone Hydrochloride Oral Solution slowly in geriatric patients and monitor closely for signs of central nervous system and respiratory depression [see Warnings and Precautions (5.6) ].

Oxycodone is known to be substantially excreted by the kidney, and the risk of adverse reactions to this drug may be greater in patients with impaired renal function. Because elderly patients are more likely to have decreased renal function, care should be taken in dose selection, and it may be useful to monitor renal function.

8.6 Hepatic Impairment

Since oxycodone is extensively metabolized in the liver, its clearance may decrease in patients with hepatic impairment. Initiate therapy in these patients with a lower than usual dosage of Oxycodone Hydrochloride Oral Solution and titrate carefully. Monitor closely for adverse events such as respiratory depression, sedation, and hypotension [see Clinical Pharmacology (12.3) ].

8.7 Renal Impairment

Information from oxycodone tablets indicate that patients with renal impairment had higher plasma concentrations of oxycodone than subjects with normal renal function.

Initiate therapy with a lower than usual dosage of Oxycodone Hydrochloride Oral Solution and titrate carefully. Monitor closely for adverse events such as respiratory depression, sedation, and hypotension [see Clinical Pharmacology (12.3) ].

9 DRUG ABUSE AND DEPENDENCE

9.1 Controlled Substance

Oxycodone Hydrochloride Oral Solution contains oxycodone, a Schedule II controlled substance.

9.2 Abuse

Oxycodone Hydrochloride Oral Solution contains oxycodone, a substance with a high potential for abuse similar to other opioids including fentanyl, hydrocodone, hydromorphone, methadone, morphine, oxymorphone, and tapentadol. Oxycodone Hydrochloride Oral Solution can be abused and is subject to misuse, addiction, and criminal diversion [see Warnings and Precautions (5.2)] .

All patients treated with opioids require careful monitoring for signs of abuse and addiction, because use of opioid analgesic products carries the risk of addiction even under appropriate medical use.

Prescription drug abuse is the intentional non-therapeutic use of a prescription drug, even once, for its rewarding psychological or physiological effects.

Drug addiction is a cluster of behavioral, cognitive, and physiological phenomena that develop after repeated substance use and includes: a strong desire to take the drug, difficulties in controlling its use, persisting in its use despite harmful consequences, a higher priority given to drug use than to other activities and obligations, increased tolerance, and sometimes a physical withdrawal.

“Drug-seeking” behavior is very common in persons with substance use disorders. Drug-seeking tactics include emergency calls or visits near the end of office hours, refusal to undergo appropriate examination, testing, or referral, repeated “loss” of prescriptions, tampering with prescriptions, and reluctance to provide prior medical records or contact information for other treating health care provider(s). “Doctor shopping” (visiting multiple prescribers to obtain additional prescriptions) is common among drug abusers and people suffering from untreated addiction. Preoccupation with achieving adequate pain relief can be appropriate behavior in a patient with poor pain control.

Abuse and addiction are separate and distinct from physical dependence and tolerance. Health care providers should be aware that addiction may not be accompanied by concurrent tolerance and symptoms of physical dependence in all addicts. In addition, abuse of opioids can occur in the absence of true addiction.

Oxycodone Hydrochloride Oral Solution, like other opioids, can be diverted for non-medical use into illicit channels of distribution. Careful record-keeping of prescribing information, including quantity, frequency, and renewal requests, as required by state and federal law, is strongly advised.

Proper assessment of the patient, proper prescribing practices, periodic re-evaluation of therapy, and proper dispensing and storage are appropriate measures that help to limit abuse of opioid drugs.

Risks Specific to Abuse of Oxycodone Hydrochloride Oral Solution

Oxycodone Hydrochloride Oral Solution is for oral use only. Abuse of oxycodone poses a risk of overdose and death. The risk is increased with concurrent abuse of alcohol and other central nervous system depressants. Parenteral drug abuse is commonly associated with transmission of infectious diseases such as hepatitis and HIV.

9.3 Dependence

Both tolerance and physical dependence can develop during chronic opioid therapy. Tolerance is the need for increasing doses of opioids to maintain a defined effect such as analgesia (in the absence of disease progression or other external factors). Tolerance may occur to both the desired and undesired effects of drugs, and may develop at different rates for different effects.

Physical dependence results in withdrawal symptoms after abrupt discontinuation or a significant dosage reduction of a drug. Withdrawal also may be precipitated through the administration of drugs with opioid antagonist activity (e.g., naloxone, nalmefene), mixed agonist/antagonist analgesics (e.g., pentazocine, butorphanol, nalbuphine), or partial agonists (e.g., buprenorphine). Physical dependence may not occur to a clinically significant degree until after several days to weeks of continued opioid usage.

Oxycodone Hydrochloride Oral Solution should not be abruptly discontinued in a physically-dependent patient [see Dosage and Administration (2.4) ] . If Oxycodone Hydrochloride Oral Solution is abruptly discontinued in a physically-dependent patient, a withdrawal syndrome may occur. Some or all of the following can characterize this syndrome: restlessness, lacrimation, rhinorrhea, yawning, perspiration, chills, myalgia, and mydriasis. Other signs and symptoms also may develop, including: irritability, anxiety, backache, joint pain, weakness, abdominal cramps, insomnia, nausea, anorexia, vomiting, diarrhea, or increased blood pressure, respiratory rate, or heart rate.

Infants born to mothers physically dependent on opioids will also be physically dependent and may exhibit respiratory difficulties and withdrawal signs [see Use in Specific Populations (8.1) ].

10 OVERDOSAGE

Clinical Presentation

Acute overdose with Oxycodone Hydrochloride Oral Solution can be manifested by respiratory depression, somnolence progressing to stupor or coma, skeletal muscle flaccidity, cold and clammy skin, constricted pupils, and, in some cases, pulmonary edema, bradycardia, hypotension, partial or complete airway obstruction, atypical snoring, and death. Marked mydriasis rather than miosis may be seen with hypoxia in overdose situations [see Clinical Pharmacology (12.2) ].

Treatment of Overdose

In case of overdose, priorities are the reestablishment of a patent and protected airway and institution of assisted or controlled ventilation, if needed. Employ other supportive measures (including oxygen and vasopressors) in the management of circulatory shock and pulmonary edema as indicated. Cardiac arrest or arrhythmias will require advanced life-support techniques.

The opioid antagonists, naloxone or nalmefene, are specific antidotes to respiratory depression resulting from opioid overdose. For clinically significant respiratory or circulatory depression secondary to oxycodone overdose, administer an opioid antagonist. Opioid antagonists should not be administered in the absence of clinically significant respiratory or circulatory depression secondary to oxycodone overdose.

Because the duration of opioid reversal is expected to be less than the duration of action of oxycodone in Oxycodone Hydrochloride Oral Solution, carefully monitor the patient until spontaneous respiration is reliably re-established. If the response to an opioid antagonist is suboptimal or only brief in nature, administer additional antagonist as directed by the product’s prescribing information.

In an individual physically dependent on opioids, administration of the recommended usual dosage of the antagonist will precipitate an acute withdrawal syndrome. The severity of the withdrawal symptoms experienced will depend on the degree of physical dependence and the dose of the antagonist administered. If a decision is made to treat serious respiratory depression in the physically dependent patient, administration of the antagonist should be initiated with care and by titration with smaller than usual doses of the antagonist.

11 DESCRIPTION

Oxycodone Hydrochloride Oral Solution is an opioid agonist, available as solution in 5 mg/5 mL (1 mg/mL) strength for oral administration.

Chemically, oxycodone hydrochloride is 4, 5α-epoxy-14-hydroxy-3-methoxy-17-methylmorphinan-6one hydrochloride and has the following structural formula:

[structure]

C18H21NO4•HCl MW 351.82

Oxycodone hydrochloride is a white, odorless crystalline powder derived from the opium alkaloid, thebaine. Oxycodone hydrochloride dissolves in water (1 g in 6 to 7 mL) and is considered slightly soluble in alcohol (octanol water partition coefficient is 0.7).

Oxycodone Hydrochloride Oral Solution, 5 mg per 5 mL contains equivalent of 4.5 mg of oxycodone free base per 5 mL's and contains the following inactive ingredients: Poloxamer 188 NF, Sodium Benzoate NF, Citric Acid Anhydrous USP, Glycerin Natural USP, Sorbitol Solution 70% USP, FD&C Red #40, Raspberry Flavor and Water.

12 CLINICAL PHARMACOLOGY

12.1 Mechanism of Action

Oxycodone is a full opioid agonist and is relatively selective for the mu-opioid receptor, although it can bind to other opioid receptors at higher doses. The principal therapeutic action of oxycodone is analgesia. Like all full opioid agonists, there is no ceiling effect for analgesia with oxycodone. Clinically, dosage is titrated to provide adequate analgesia and may be limited by adverse reactions, including respiratory and CNS depression.

The precise mechanism of the analgesic action is unknown. However, specific CNS opioid receptors for endogenous compounds with opioid-like activity have been identified throughout the brain and spinal cord and are thought to play a role in the analgesic effects of this drug.

12.2 Pharmacodynamics

Effects on Central Nervous System (CNS)
Oxycodone produces respiratory depression by direct action on brain stem respiratory centers. The respiratory depression involves a reduction in the responsiveness of the brain stem respiratory centers to both increases in carbon dioxide tension and to electrical stimulation.
Oxycodone causes miosis, even in total darkness. Pinpoint pupils are a sign of opioid overdose but are not pathognomonic (e.g., pontine lesions of hemorrhagic or ischemic origins may produce similar findings). Marked mydriasis rather than miosis may be seen due to hypoxia in overdose situations.

Effects on the Gastrointestinal Tract and Other Smooth Muscle

Oxycodone causes a reduction in motility associated with an increase in smooth muscle tone in the antrum of the stomach and duodenum. Digestion of food in the small intestine is delayed and propulsive contractions are decreased. Propulsive peristaltic waves in the colon are decreased, while tone may be increased to the point of spasm resulting in constipation. Other opioid-induced effects may include a reduction in biliary and pancreatic secretions, spasm of sphincter of Oddi, and transient elevations in serum amylase.

Effects on the Cardiovascular System

Oxycodone produces peripheral vasodilation which may result in orthostatic hypotension or syncope. Manifestations of histamine release and/or peripheral vasodilation may include pruritus, flushing, red eyes and sweating and/or orthostatic hypotension.

Effects on the Endocrine System

Opioids inhibit the secretion of adrenocorticotropic hormone (ACTH), cortisol, and luteinizing hormone (LH) in humans [see Adverse Reactions (6) ]. They also stimulate prolactin, growth hormone (GH) secretion, and pancreatic secretion of insulin and glucagon.

Chronic use of opioids may influence the hypothalamic-pituitary-gonadal axis, leading to androgen deficiency that may manifest as low libido, impotence, erectile dysfunction, amenorrhea, or infertility. The causal role of opioids in the clinical syndrome of hypogonadism is unknown because the various medical, physical, lifestyle, and psychological stressors that may influence gonadal hormone levels have not been adequately controlled for in studies conducted to date [see Adverse Reactions (6) ].

Effects on the Immune System

Opioids have been shown to have a variety of effects on components of the immune system in in vitro and animal models. The clinical significance of these findings is unknown. Overall, the effects of opioids appear to be modestly immunosuppressive.

Concentration–Efficacy Relationships

The minimum effective analgesic concentration will vary widely among patients, especially among patients who have been previously treated with potent agonist opioids. The minimum effective analgesic concentration of oxycodone for any individual patient may increase over time due to an increase in pain, the development of a new pain syndrome and/or the development of analgesic tolerance [see Dosage and Administration (2.1, 2.2) ].

Concentration–Adverse Reaction Relationships

There is a relationship between increasing oxycodone plasma concentration and increasing frequency of dose-related opioid adverse reactions such as nausea, vomiting, CNS effects, and respiratory depression. In opioid-tolerant patients, the situation may be altered by the development of tolerance to opioid-related adverse reactions [see Dosage and Administration (2.1, 2.2, 2.3) ].

12.3 Pharmacokinetics

The activity of Oxycodone Hydrochloride Oral Solution is primarily due to the parent drug oxycodone.

Absorption

The oral bioavailability of oxycodone is 60 - 87%. This high oral bioavailability (compared to other oral opioids) is due to lower pre-systemic and/or first-pass metabolism of oxycodone.

Food Effect

Presence of food may slightly delay the rate (C max and T max) and enhance the extent of absorption (AUC) of oxycodone from Oxycodone Hydrochloride Oral Solution. Overall, food is not expected to have a clinically significant impact on the absorption of Oxycodone Hydrochloride Oral Solution.

Distribution

Following intravenous administration, the volume of distribution (Vss) for oxycodone was 2.6 L/kg. Plasma protein binding of oxycodone at 37°C and a pH of 7.4 was about 45%. Oxycodone has been found in breast milk [seeUse in Specific Populations (8.2) ].

Elimination

Metabolism

Oxycodone hydrochloride is extensively metabolized to noroxycodone, oxymorphone, noroxymorphone, which are subsequently glucuronidated. CYP3A4 mediated N-demethylation to noroxycodone is the primary metabolic pathway of oxycodone with a less contribution from CYP2D6 mediated O-demethylation to oxymorphone. Therefore, the formation of these and related metabolites can, in theory, be affected by other drugs. The major circulating metabolite is noroxycodone with an AUC ratio of 0.6 relative to that of oxycodone. Noroxycodone is reported to be a considerably weaker analgesic than oxycodone. Oxymorphone, although possessing analgesic activity, is present in the plasma only in low concentrations. The correlation between oxymorphone concentrations and opioid effects was much less than that seen with oxycodone plasma concentrations. The analgesic activity profile of other metabolites is not known.

Excretion

Oxycodone and its metabolites are excreted primarily via the kidney. The amounts measured in the urine have been reported as follows: free oxycodone up to 19%; conjugated oxycodone up to 50%; free oxymorphone 0%; conjugated oxymorphone ≤ 14%; both free and conjugated noroxycodone have been found in the urine but not quantified. The total plasma clearance was 0.8 L/min for adults. Apparent elimination half-life of oxycodone following the administration of Oxycodone Hydrochloride Oral Solution was approximately 3.5 hours.

Special Populations

Age: Geriatric Population

Information obtained from oxycodone tablets indicate that the plasma concentrations of oxycodone did not appear to be increased in patients over of the age of 65.

Hepatic Impairment

Because oxycodone is extensively metabolized in the liver, its clearance may decrease in hepatic-impaired patients. A dose adjustment is recommended in these patients [see Use in Special Populations (8.6) ] .

Renal Impairment

Because this drug is known to be substantially excreted by the kidney, and the risk of adverse reactions to this drug may be greater in patients with impaired renal function, a dose reduction is recommended for renal impaired patients. [see Use in Special Populations (8.7) ] .

Drug Interactions Studies

CYP3A4 Inhibitors

CYP3A4 is the major enzyme involved in noroxycodone formation. A published study showed that the co-administration of voriconazole, a CYP3A4 inhibitor, increased oxycodone AUC and C max by 3.6 and 1.7 fold, respectively.

CYP3A4 Inducers

A published study showed that the co-administration of rifampin, a drug metabolizing enzyme inducer, decreased oxycodone AUC and C max values by 86% and 63%, respectively.

CYP2D6 Inhibitors

Oxycodone is metabolized in part to oxymorphone via the cytochrome p450 isoenzyme CYP2D6. While this pathway may be blocked by a variety of drugs (e.g., certain cardiovascular drugs and antidepressants), such blockade has not yet been shown to be of clinical significance with this agent.

13 NONCLINICAL TOXICOLOGY

13.1 Carcinogenesis, Mutagenesis, Impairment of Fertility

Carcinogenesis

Long-term animal studies to evaluate the carcinogenic potential of oxycodone have not been conducted.

Mutagenesis

Oxycodone hydrochloride was genotoxic in an in vitro mouse lymphoma assay in the presence of metabolic activation. There was no evidence of genotoxic potential in an in vitro bacterial reverse mutation assay (Salmonella typhimurium and Escherichia coli) or in an assay for chromosomal aberrations (in vivo mouse bone marrow micronucleus assay).

Impairment of Fertility

The potential effects of oxycodone on male and female fertility have not been evaluated.

16 HOW SUPPLIED/STORAGE AND HANDLING

Oxycodone Hydrochloride Oral Solution, USP, 5 mg per 5 mL (1 mg/mL) is available as follows:

NDC 66689-403-16: 500 mL bottle packaged with calibrated measuring cup

NDC 66689-401-01: 5 mL unit dose cup

NDC 66689-401-50: Case contains 50 unit-dose cups of 5 mL (NDC 66689-401-01), packaged in 5 trays of 10 unit-dose cups each

Dispense in a tight, light-resistant container as defined in the USP/NF.

Store at controlled room temperature 20°-25°C (68°- 77°F); excursions are permitted to 15° - 30°C (59° - 86°F). [See USP Controlled Room Temperature]

17 PATIENT COUNSELING INFORMATION

Advise the patient to read the FDA-approved patient labeling (Medication Guide).

Medication Errors

Advise patients that oxycodone hydrochloride oral solution, is available in multiple concentrations. Inform patients about which concentration they have been prescribed. Instruct patients how to measure and take the correct dose of Oxycodone Hydrochloride Oral Solution, and to always use the enclosed cup when administering Oxycodone Hydrochloride Oral Solution to ensure the dose is measured and administered accurately [see Warnings and Precautions (5.1) ].

If the prescribed concentration is changed, instruct patients on how to correctly measure the new dose to avoid errors which could result in accidental overdose and death.

Addiction, Abuse, and Misuse

Inform patients that the use of Oxycodone Hydrochloride Oral Solution, even when taken as recommended, can result in addiction, abuse, and misuse, which can lead to overdose and death [seeWarnings and Precautions (5.2) ] .Instruct patients not to share Oxycodone Hydrochloride Oral Solution with others and to take steps to protect Oxycodone Hydrochloride Oral Solution from theft or misuse.

Life-Threatening Respiratory Depression

Inform patients of the risk of life-threatening respiratory depression, including information that the risk is greatest when starting Oxycodone Hydrochloride Oral Solution or when the dosage is increased, and that it can occur even at recommended dosages [see Warnings and Precautions (5.3) ]. Advise patients how to recognize respiratory depression and to seek medical attention if breathing difficulties develop.

Accidental Ingestion

Inform patients that accidental ingestion, especially by, children, may result in respiratory depression or death [see Warnings and Precautions (5.3) ]. Instruct patients to take steps to store Oxycodone Hydrochloride Oral Solution securely and to dispose of unused Oxycodone Hydrochloride Oral Solution by flushing the solution down the toilet.

Interactions with Benzodiazepines and Other CNS Depressants

Inform patients and caregivers that potentially fatal additive effects may occur if Oxycodone Hydrochloride Oral Solution is used with benzodiazepines or other CNS depressants, including alcohol, and not to use these concomitantly unless supervised by a health care provider [see Warnings and Precautions (5.6), Drug Interactions (7) ] .

Serotonin Syndrome

Inform patients that opioids could cause a rare but potentially life-threatening condition resulting from concomitant administration of serotonergic drugs. Warn patients of the symptoms of serotonin syndrome and to seek medical attention right away if symptoms develop. Instruct patients to inform their healthcare providers if they are taking, or plan to take serotonergic medications. [see Drug Interactions (7) ].

MAOI Interaction

Inform patients to avoid taking Oxycodone Hydrochloride Oral Solution while using any drugs that inhibit monoamine oxidase. Patients should not start MAOIs while taking Oxycodone Hydrochloride Oral Solution [see Drug Interactions (7) ].

Adrenal Insufficiency

Inform patients that opioids could cause adrenal insufficiency, a potentially life-threatening condition. Adrenal insufficiency may present with non-specific symptoms and signs such as nausea, vomiting, anorexia, fatigue, weakness, dizziness, and low blood pressure. Advise patients to seek medical attention if they experience a constellation of these symptoms [see Warnings and Precautions (5.8) ].

Important Administration Instructions

Instruct patients how to properly take Oxycodone Hydrochloride Oral Solution. [see Dosage and Administration (2.1), Warnings and Precautions (5.1) ]

Advise patients to always use the enclosed calibrated dosing cup when administering Oxycodone Hydrochloride Oral Solution to ensure the dose is measured and administered accurately [see Warnings and Precautions (5.1) ].
Advise patients never to use household teaspoons or tablespoons to measure Oxycodone Hydrochloride Oral Solution.
Advise patients not to adjust the dose of Oxycodone Hydrochloride Oral Solution without consulting with a physician or other healthcare provider.

If patients have been receiving treatment with Oxycodone Hydrochloride Oral Solution for more than a few weeks and cessation of therapy is indicated, counsel them on the importance of safely tapering the dose as abrupt discontinuation of the medication could precipitate withdrawal symptoms. Provide a dose schedule to accomplish a gradual discontinuation of the medication [see Dosage and Administration (2.4) ].

Hypotension

Inform patients that Oxycodone Hydrochloride Oral Solution may cause orthostatic hypotension and syncope. Instruct patients how to recognize symptoms of low blood pressure and how to reduce the risk of serious consequences should hypotension occur (e.g., sit or lie down, carefully rise from a sitting or lying position) [see Warnings and Precautions (5.9) ].

Anaphylaxis

Inform patients that anaphylaxis has been reported with ingredients contained in Oxycodone Hydrochloride Oral Solution. Advise patients how to recognize such a reaction and when to seek medical attention [see Contraindications (4), Adverse Reactions (6) ] .

Pregnancy

Neonatal Opioid Withdrawal Syndrome

Inform female patients of reproductive potential that prolonged use of Oxycodone Hydrochloride Oral Solution during pregnancy can result in neonatal opioid withdrawal syndrome, which may be life-threatening if not recognized and treated[see Warnings and Precautions (5.4), Use in Specific Populations (8.1) ] .

Embryo-Fetal Toxicity

Inform female patients of reproductive potential that Oxycodone Hydrochloride Oral Solution can (or may) cause fetal harm and to inform the healthcare provider of a known or suspected pregnancy [see Use in Specific Populations (8.1) ] .

Lactation

Advise nursing mothers to monitor infants for increased sleepiness (more than usual), breathing difficulties, or limpness. Instruct nursing mothers to seek immediate medical care if they notice these signs [see Use in Specific Populations (8.2) ].

Infertility

Inform patients that chronic use of opioids may cause reduced fertility. It is not known whether these effects on fertility are reversible [see Use in Specific Populations (8.3) ] .

Driving or Operating Heavy Machinery

Inform patients that Oxycodone Hydrochloride Oral Solution may impair the ability to perform potentially hazardous activities such as driving a car or operating heavy machinery. Advise patients not to perform such tasks until they know how they will react to the medication [see Warnings and Precautions (5.14) ].

Constipation

Advise patients of the potential for severe constipation, including management instructions and when to seek medical attention [see Adverse Reactions (6), Clinical Pharmacology (12.2) ] .

Disposal of Unused Oxycodone Hydrochloride Oral Solution

Advise patients to dispose of unused Oxycodone Hydrochloride Oral Solution by flushing the solution down the toilet or disposing of in accordance with local guidelines and/or regulations.

SPL UNCLASSIFIED SECTION

Manufactured by:
VistaPharm ®
Largo, FL 33771

VP 2013R2
12/2016

To request medical information contact VistaPharm, Inc. at 1-727-530-1633.

MEDICATION GUIDE OXYCODONE (OX-EE-CO-DOHN) HYDROCHLORIDE ORAL SOLUTION, CII

Oxycodone Hydrochloride Oral Solution is:

A strong prescription pain medicine that contains an opioid (narcotic) that is used to manage pain severe enough to require an opioid pain medicine, when other pain treatments such as non-opioid pain medicines do not treat your pain well enough or you cannot tolerate them.
An opioid pain medicine that can put you at risk for overdose and death. Even if you take your dose correctly as prescribed you are at risk for opioid addiction, abuse, and misuse that can lead to death.

Important information about Oxycodone Hydrochloride Oral Solution:

Get emergency help right away if you take too much Oxycodone Hydrochloride Oral Solution (overdose). When you first start taking Oxycodone Hydrochloride Oral Solution, when your dose is changed, or if you take too much (overdose), serious or life-threatening breathing problems that can lead to death may occur.
Taking Oxycodone Hydrochloride Oral Solution with other opioid medicines, benzodiazepines, alcohol, or other central nervous system depressants (including street drugs) can cause severe drowsiness, decreased awareness, breathing problems, coma, and death.
Never give anyone else your Oxycodone Hydrochloride Oral Solution. They could die from taking it. Store Oxycodone Hydrochloride Oral Solution away from children and in a safe place to prevent stealing or abuse. Selling or giving away Oxycodone Hydrochloride Oral Solution is against the law.

Do not take Oxycodone Hydrochloride Oral Solution if you have:

severe asthma, trouble breathing, or other lung problems.
a bowel blockage or have narrowing of the stomach or intestines.
an allergy to oxycodone or any of the ingredients in Oxycodone Hydrochloride Oral Solution.

Before taking Oxycodone Hydrochloride Oral Solution, tell your healthcare provider if you have a history of:

head injury, seizures · liver, kidney, thyroid problems
problems urinating · pancreas or gallbladder problems
abuse of street or prescription drugs, alcohol addiction, or mental health problems.

Tell your healthcare provider if you are:

pregnant or planning to become pregnant. Prolonged use of Oxycodone Hydrochloride Oral Solution during pregnancy can cause withdrawal symptoms in your newborn baby that could be life-threatening if not recognized and treated.
breastfeeding. Oxycodone Hydrochloride Oral Solution passes into breast milk and may harm your baby.
taking prescription or over-the-counter medicines, vitamins, or herbal supplements. Taking Oxycodone Hydrochloride Oral Solution with certain other medicines can cause serious side effects that could lead to death.

When taking Oxycodone Hydrochloride Oral Solution:

Do not change your dose. Take Oxycodone Hydrochloride Oral Solution exactly as prescribed by your healthcare provider. Use the lowest dose possible for the shortest time needed.
Always use the syringe that comes with Oxycodone Hydrochloride Oral Solution to correctly measure your dose. Never use a household teaspoon or tablespoon to measure Oxycodone Hydrochloride Oral Solution.
Take your prescribed dose every 4-6 hours. Do not take more than your prescribed dose. If you miss a dose, take your next dose at your usual time.
Call your healthcare provider if the dose you are taking does not control your pain.
If you have been taking Oxycodone Hydrochloride Oral Solution regularly, do not stop taking Oxycodone Hydrochloride Oral Solution without talking to your healthcare provider.
After you stop taking Oxycodone Hydrochloride Oral Solution, flush the remaining medication down the toilet.

While taking Oxycodone Hydrochloride Oral SolutionDO NOT:

Drive or operate heavy machinery, until you know how Oxycodone Hydrochloride Oral Solution affects you. Oxycodone Hydrochloride Oral Solution can make you sleepy, dizzy, or lightheaded.
Drink alcohol or use prescription or over-the-counter medicines that contain alcohol. Using products containing alcohol during treatment with Oxycodone Hydrochloride Oral Solution may cause you to overdose and die.

The possible side effects of Oxycodone Hydrochloride Oral Solution:

constipation, nausea, sleepiness, vomiting, tiredness, headache, dizziness, abdominal pain. Call your healthcare provider if you have any of these symptoms and they are severe.

Get emergency medical help if you have:

trouble breathing, shortness of breath, fast heartbeat, chest pain, swelling of your face, tongue, or throat, extreme drowsiness, light-headedness when changing positions, feeling faint, agitation, high body temperature, trouble walking, stiff muscles, or mental changes such as confusion.

These are not all the possible side effects of Oxycodone Hydrochloride Oral Solution. Call your doctor for medical advice about side effects. You may report side effects to FDA at 1-800-FDA-1088. For more information, go to dailymed.nlm.nih.gov.

Manufactured by: VistaPharm, Inc., Largo, Florida

WWW.VISTAPHARM.COM or call 1-727-530-1633

This medication Guide has been approved by the U.S. Food and Drug Administration 12/16

Manufactured by:

VistaPharm®

Largo, FL 33771

VP2100R1

12/16

Rx Only